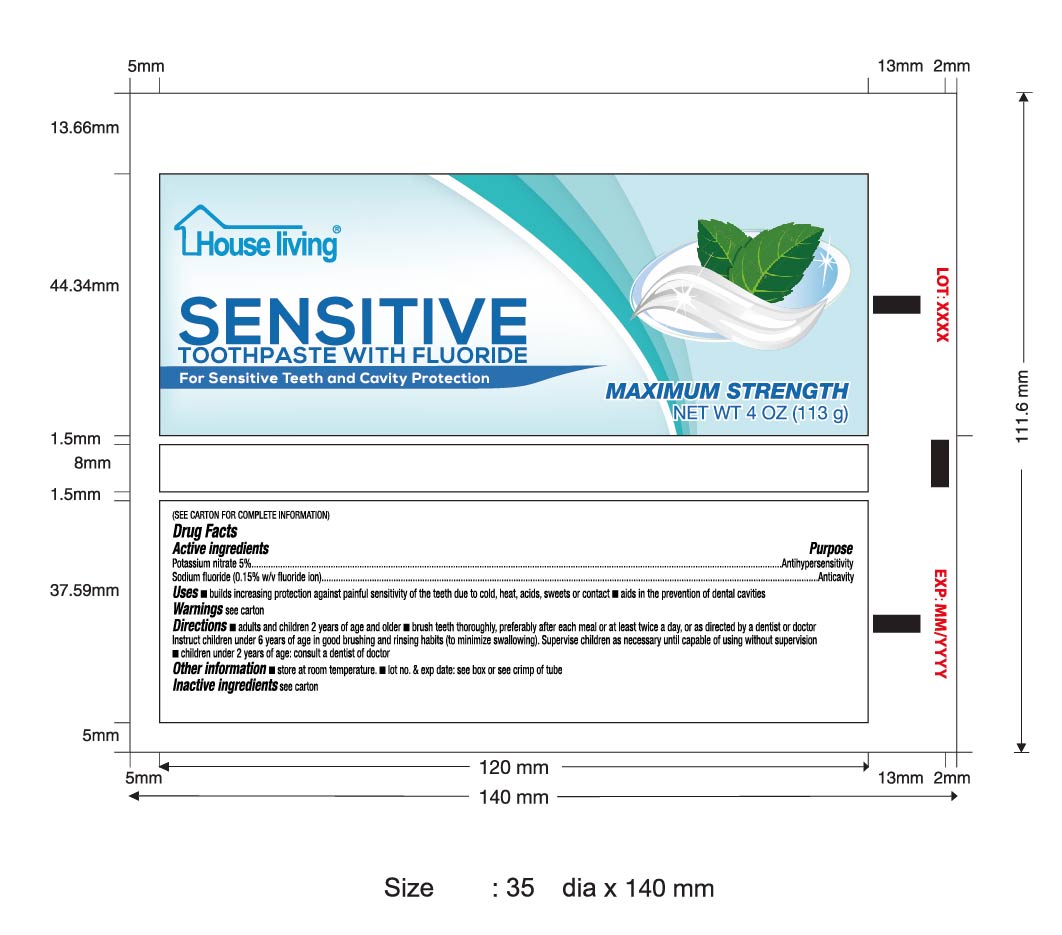 DRUG LABEL: House Living
NDC: 71704-002 | Form: PASTE
Manufacturer: Guangzhou Beauty Cosmetic Co., Ltd
Category: otc | Type: HUMAN OTC DRUG LABEL
Date: 20170913

ACTIVE INGREDIENTS: POTASSIUM NITRATE 5 g/100 g; SODIUM FLUORIDE 0.15 g/100 g
INACTIVE INGREDIENTS: PEG/PPG-116/66 COPOLYMER; SACCHARIN SODIUM; WATER; SORBITOL; SILICON DIOXIDE; SODIUM LAURYL SULFATE; POLYETHYLENE GLYCOL 300; CARBOXYMETHYLCELLULOSE SODIUM; SODIUM PYROPHOSPHATE DECAHYDRATE; TITANIUM DIOXIDE; SODIUM HYDROXIDE

Active Ingredient

SODIUM FLUORIDE 0.15%

Potassium Nitrate 5%

Purpose

Antihypersensitivity

Anticavity

Use

bulids increasing protection against painful sensitivity of the teeth due to cold,heat,acids,sweets or contact

aids in the privention of dental cavities

Warning

Stop use and ask a dentist if

the problem pensists os worsens,sensitive teeth may indicate a serious problem that may prompt care by a dentist

pain/sensitivity still persists after 4 weeks of use.

Directions

Adults and children 2 years of age and older:brush teeth thoroughly, preferably after meals or at least twice a day or use as directed by a dentist or doctor.

instruct children 6 years of age in good brushing and rinsing habits(to minimize swallowing)

suprevise children as necessary untill capable of using without supervision.

children under 2 years of age :consult a dentist or doctor

Inactive Ingredients

Water,Silica (Thickening 10 & Friction 4)
,Sodium Lauryl Alcohol,Sorbitol,Polyethylene Glycol 300,Sodium Carboxymethylcellulose,Flavor,Sodium Saccharin,Titanium Dioxide,Sodium Pyrophosphate,PEG/PPG 116/66 copolymer
Sodium Hydroxide,Acid Yellow 23,Acid Blue 1

Keep out of reach of children under 6 years of age.
If more than used for brushing is accidently swallowed get medical help or contact a poison control center right away.